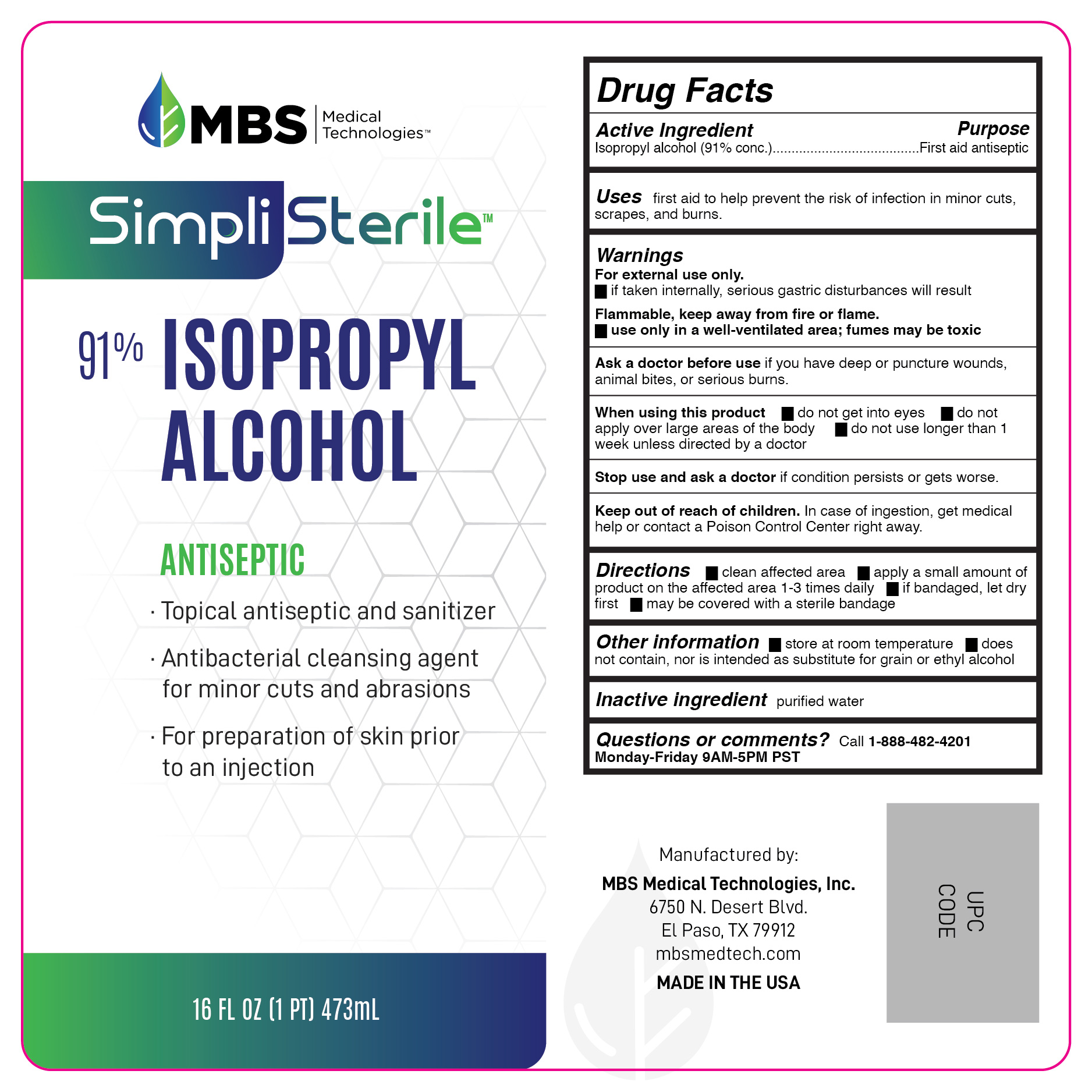 DRUG LABEL: 91% Isopropyl Alcohol
NDC: 79590-003 | Form: LIQUID
Manufacturer: MBS Medical Technologies
Category: otc | Type: HUMAN OTC DRUG LABEL
Date: 20200916

ACTIVE INGREDIENTS: ISOPROPYL ALCOHOL 91 mL/100 mL
INACTIVE INGREDIENTS: WATER

91% Isopropyl Alcohol

DOSAGE AND ADMINISTRATION

clean affected area, apply a small amount of the this product to the affected area 1 to 3 times daily, bandage.

ACTIVE INGREDIENT

Isopropyl Alcohol 91%

PURPOSE

First Aid Antiseptic

ASK DOCTOR

if you have deep or puncture wounds, animal bites or serious burns

WHEN USING

do not get into eyes, do not inhale, do not apply over large area of body

STOP USE

condition persists or gets worse

KEEP OUT OF REACH OF CHILDREN

if swallowed, get medical help or contact a Poison Prevention Center immediately

OTHER SAFETY INFORMATION

does not contain, nor is intended as a substitute for grain or ethyl alcohol

fumes can be acutely irritating to the skin, eyes, and the respiratory system

INDICATIONS AND USAGE

First aid to help prevent the risk of infection in: minor cuts, scrapes, burns

INACTIVE INGREDIENT

deionized water

WARNINGS

for external use only. If taken internally serious gastric disturbances will result. Flammable. Keep away from heat, flame, electrical.